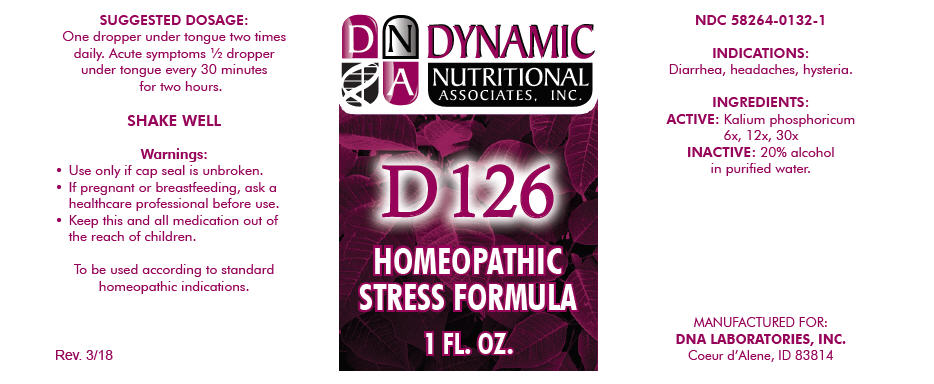 DRUG LABEL: D-126
NDC: 58264-0132 | Form: SOLUTION
Manufacturer: DNA Labs, Inc.
Category: homeopathic | Type: HUMAN OTC DRUG LABEL
Date: 20250113

ACTIVE INGREDIENTS: DIBASIC POTASSIUM PHOSPHATE 6 [hp_X]/1 mL
INACTIVE INGREDIENTS: ALCOHOL; WATER

D-126

NDC 58264-0132-1

INDICATIONS

PURPOSE

Diarrhea, headaches, hysteria.

INGREDIENTS

ACTIVE

Kalium phosphoricum 6x, 12x, 30x

INACTIVE

20% alcohol in purified water.

SUGGESTED DOSAGE

One dropper under tongue two times daily. Acute symptoms ½ dropper under tongue every 30 minutes for two hours.

STORAGE AND HANDLING

SHAKE WELL

Warnings

- Use only if cap seal is unbroken.

PREGNANCY OR BREAST FEEDING

- If pregnant or breastfeeding, ask a healthcare professional before use.

KEEP OUT OF REACH OF CHILDREN

- Keep this and all medication out of the reach of children.

To be used according to standard homeopathic indications.

PRINCIPAL DISPLAY PANEL - 1 FL. OZ. Bottle Label

DYNAMIC
NUTRITIONAL
ASSOCIATES, INC.

D 126

HOMEOPATHIC
STRESS FORMULA

1 FL. OZ.